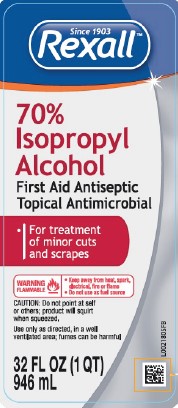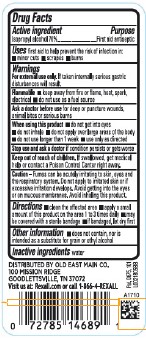 DRUG LABEL: 70%
NDC: 55910-810 | Form: LIQUID
Manufacturer: Old East Main Co.
Category: otc | Type: HUMAN OTC DRUG LABEL
Date: 20260302

ACTIVE INGREDIENTS: ISOPROPYL ALCOHOL 70 mL/100 mL
INACTIVE INGREDIENTS: WATER

Rexall 810.003/810AA
70% Isopropyl Alcohol

Active ingredient

Isopropyl alcohol 70%

Purpose

First Aid Antiseptic

Uses

first aid to help prevent the risk of infection in:

- minor cuts
- scrapes
- burns

Warnings

For external use only. If taken internally serious gastric disturbances will result.

Flammable

- Keep away from fire or flame, heat, spark, electrical
- Do not use as a fuel source

Ask a doctor before use

for deep or puncture wounds, animal bites or serious burns

When using this product

- do not get into eyes
- do not inhale
- do not apply over large areas of the body
- do not use longer than 1 week
- use only as directed

Stop use and ask a doctor

If condition persists or gets worse

Keep out of reach of children.

If swallowed, get medical help or contact a Poison Control Center right away.

Caution

Fumes can be acutely irritating to skin, eyes and the respiratory system. Do not apply to irritated skin or if excessive irritation develops. Avoid getting into the eyes or on mucous membranes. Avoid inhaling this product.

Directions

- clean the affected area
- apply a small amount of this product on the affected area 1 to 3 times daily
- may be covered with a sterile bandage
- if bandaged, let dry first

Other information

• does not contain, nor is intended as a substitute for grain or ethyl alcohol

Inactive ingredient

water

Adverse Reaction

DISTRIBUTED BY OLD EAST MAIN CO.

100 MISSION RIDGE

GOODLETTSVILLE, TN 37072

Visit us at: Rexall.com or call 1-866-4-REXALL

Pat. D675, 101

principal display panel

Since 1903

Rexall™

70% Isopropyl Alcohol

First Aid Antiseptic

Topical Antimicrobial

- For treatment of minor cuts and scrapes

WARNING FLAMMABLE

- Keep away from heat, spark, electric, fire or flame
- Do not use as fuel source

CAUTION: Do not point at self or others; product will squirt when squeezed.

Use only as directed, in a well-ventilated area; fumes can be harmful.

32 FL OZ (1 QT) 946 mL